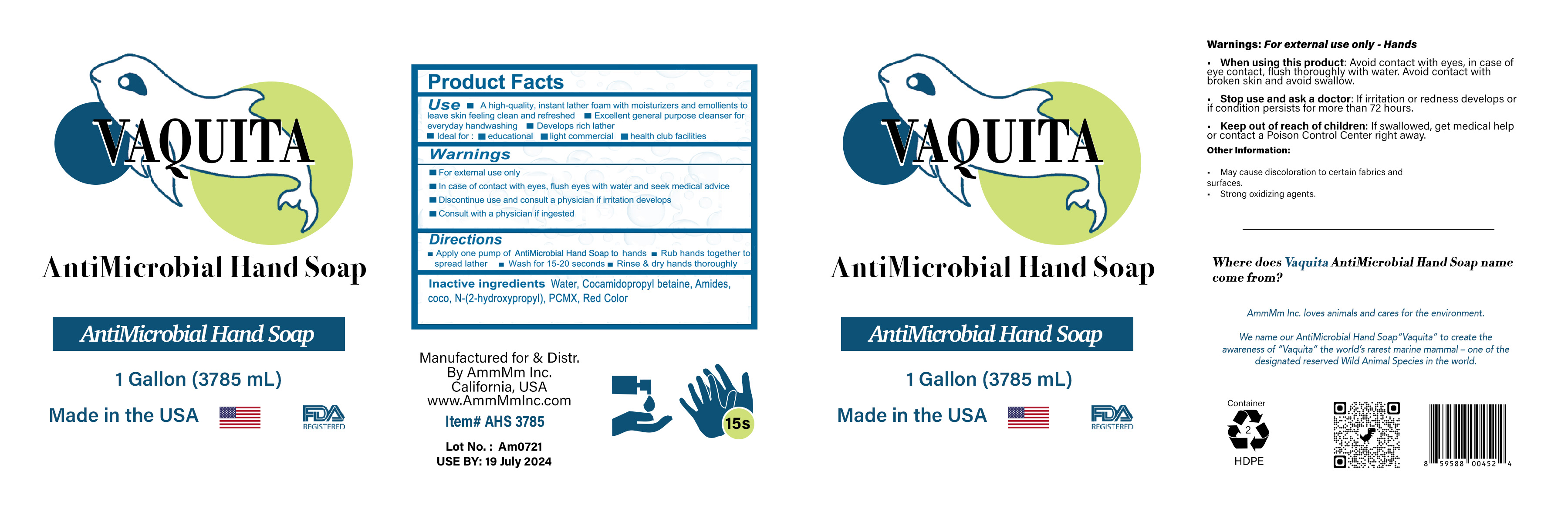 DRUG LABEL: ANTIMICROBIAL HAND
NDC: 77397-103 | Form: SOAP
Manufacturer: AMMMM INC
Category: otc | Type: HUMAN OTC DRUG LABEL
Date: 20210721

ACTIVE INGREDIENTS: CHLOROXYLENOL 0.3 g/100 mL
INACTIVE INGREDIENTS: WATER; SODIUM LAURETH SULFATE; COCAMIDOPROPYL BETAINE; POLYQUATERNIUM-7 (70/30 ACRYLAMIDE/DADMAC; 1600 KD); ANHYDROUS CITRIC ACID; D&C RED NO. 33

AMMMM - VAQUITA ANTI-MICROBIAL HAND SOAP (Chloroxylenol 0.04%)

ACTIVE INGREDIENT

CHLOROXYLENOL 0.04%

PURPOSE

ANTIMICROBIAL

USES

- A HIGH QUALITY, INSTANT LATHER FOAM WITH MOISTURIZERS AND EMOLLIENTS TO LEAVE SKIN FEELING CLEAN AND REFRESHED.
- EXCELLENT GENERAL PURPOSE CLEANSER FOR EVERYDAY HAND WASHING.
- DEVELOPS RICH LATHER.
- IDEAL FOR:
- EDUCATIONAL
- LIGHT COMMERCIAL
- HEALTH CLUB FACILITIES

WARNINGS

FOR EXTERNAL USE ONLY.

IN CASE OF CONTACT WITH EYES, FLUSH EYES WITH WATER AND SEEK MEDICAL ADVICE.

DISCONTINUE USE AND CONSULT A PHYSICIAN IF IRRITATION DEVELOPS.

CONSULT WITH A PHYSICIAN IF INGESTED.

KEEP OUT OF REACH OF CHILDREN. IF SWALLOWED, GET MEDICAL HELP OR CONTACT A POISON CONTROL CENTER RIGHT AWAY.

DIRECTIONS

- APPLY ONE PUMP OF ANTIMICROBIAL HAND SOAP TO HANDS.
- RUB HANDS TOGETHER TO SPREAD LATHER.
- WASH FOR 15-20 SECONDS.
- RINSE AND DRY HANDS THOROUGHLY.

INACTIVE INGREDIENTS

WATER, COCAMIDOPROPYL BETAINE, AMIDES, COCO, N-(2-HYDROXYPROPYL), PCMX, RED COLOR